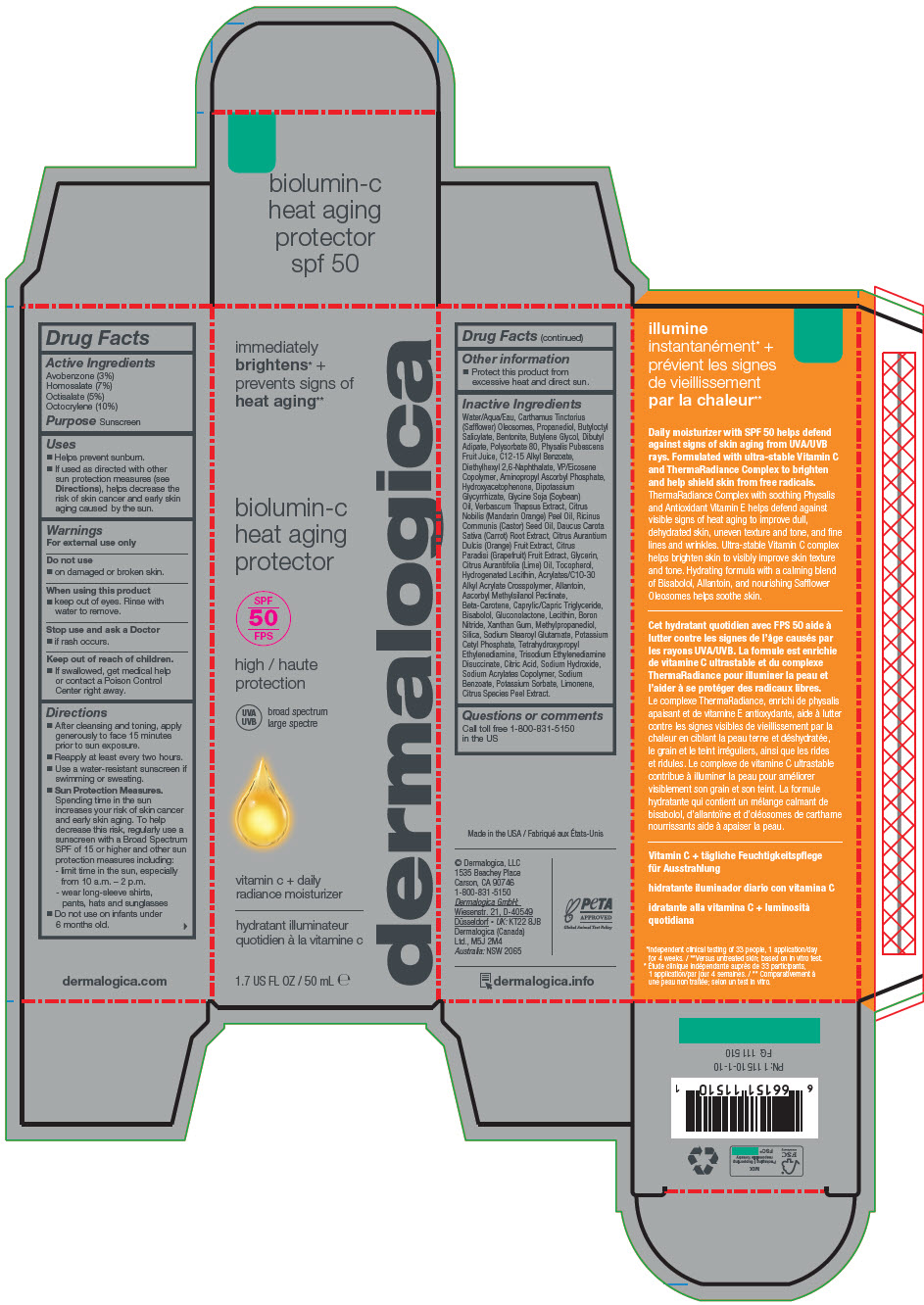 DRUG LABEL: BIOLUMIN-C HEAT AGING PROTECTOR SPF50
NDC: 68479-371 | Form: LOTION
Manufacturer: Dermalogica, LLC.
Category: otc | Type: HUMAN OTC DRUG LABEL
Date: 20241016

ACTIVE INGREDIENTS: Octocrylene 10 g/100 mL; Homosalate 7 g/100 mL; Octisalate 5 g/100 mL; Avobenzone 3 g/100 mL
INACTIVE INGREDIENTS: Water; SAFFLOWER OIL; Propanediol; Butyloctyl Salicylate; Bentonite; Butylene Glycol; Dibutyl Adipate; Polysorbate 80; Physalis Pubescens Fruit Juice; ALKYL (C12-15) BENZOATE; Diethylhexyl 2,6-Naphthalate; VINYLPYRROLIDONE/EICOSENE COPOLYMER; MEDIUM-CHAIN TRIGLYCERIDES; HYDROGENATED SOYBEAN LECITHIN; Potassium Cetyl Phosphate; SILICON DIOXIDE; Boron Nitride; Aminopropyl Ascorbyl Phosphate; Hydroxyacetophenone; Glycerin; EDETOL; CITRIC ACID MONOHYDRATE; Allantoin; LEVOMENOL; Gluconolactone; SOYBEAN LECITHIN; SOYBEAN OIL; Tocopherol; Xanthan Gum; Sodium Hydroxide; Sodium Stearoyl Glutamate; VERBASCUM THAPSUS WHOLE; Trisodium Ethylenediamine Disuccinate; Methylpropanediol; GLYCYRRHIZINATE DIPOTASSIUM; Sodium Benzoate; ORANGE; MANDARIN OIL; GRAPEFRUIT OIL; CASTOR OIL; LIME OIL, DISTILLED; ORANGE PEEL; Ascorbyl Methylsilanol Pectinate; Potassium Sorbate; BETA CAROTENE; CARROT; LIMONENE, (+)-

BIOLUMIN-C HEAT AGING PROTECTOR SPF50

Drug Facts

Active Ingredients

Avobenzone (3%)
Homosalate (7%)
Octisalate (5%)
Octocrylene (10%)

Purpose

Sunscreen

Uses

- Helps prevent sunburn.
- If used as directed with other sun protection measures (see Directions), helps decrease the risk of skin cancer and early skin aging caused by the sun.

Warnings

For external use only

Do not use

- on damaged or broken skin.

When using this product

- keep out of eyes. Rinse with water to remove.

Stop use and ask a Doctor

- if rash occurs.

Keep out of reach of children.

- If swallowed, get medical help or contact a Poison Control Center right away.

Directions

- After cleansing and toning, apply generously to face 15 minutes prior to sun exposure.
- Reapply at least every two hours.
- Use a water-resistant sunscreen if swimming or sweating.
- Sun Protection Measures. Spending time in the sun increases your risk of skin cancer and early skin aging. To help decrease this risk, regularly use a sunscreen with a Broad Spectrum SPF of 15 or higher and other sun protection measures including:
  - limit time in the sun, especially from 10 a.m. – 2 p.m.
  - wear long-sleeve shirts, pants, hats and sunglasses
- Do not use on infants under 6 months old.

Other information

- Protect this product from excessive heat and direct sun.

Inactive Ingredients

Water/Aqua/Eau, Carthamus Tinctorius (Safflower) Oleosomes, Propanediol, Butyloctyl Salicylate, Bentonite, Butylene Glycol, Dibutyl Adipate, Polysorbate 80, Physalis Pubescens Fruit Juice, C12-15 Alkyl Benzoate, Diethylhexyl 2,6-Naphthalate, VP/Eicosene Copolymer, Aminopropyl Ascorbyl Phosphate, Hydroxyacetophenone, Dipotassium Glycyrrhizate, Glycine Soja (Soybean) Oil, Verbascum Thapsus Extract, Citrus Nobilis (Mandarin Orange) Peel Oil, Ricinus Communis (Castor) Seed Oil, Daucus Carota Sativa (Carrot) Root Extract, Citrus Aurantium Dulcis (Orange) Fruit Extract, Citrus Paradisi (Grapefruit) Fruit Extract, Glycerin, Citrus Aurantifolia (Lime) Oil, Tocopherol, Hydrogenated Lecithin, Acrylates/C10-30 Alkyl Acrylate Crosspolymer, Allantoin, Ascorbyl Methylsilanol Pectinate, Beta-Carotene, Caprylic/Capric Triglyceride, Bisabolol, Gluconolactone, Lecithin, Boron Nitride, Xanthan Gum, Methylpropanediol, Silica, Sodium Stearoyl Glutamate, Potassium Cetyl Phosphate, Tetrahydroxypropyl Ethylenediamine, Trisodium Ethylenediamine Disuccinate, Citric Acid, Sodium Hydroxide, Sodium Acrylates Copolymer, Sodium Benzoate, Potassium Sorbate, Limonene, Citrus Species Peel Extract.

Questions or comments

Call toll free 1-800-831-5150 in the US

PRINCIPAL DISPLAY PANEL - 50 mL Bottle Carton

immediately
brightens* +
prevents signs of
heat aging**

biolumin-c
heat aging
protector

SPF
50

high
protection

UVA
UVB
broad spectrum

vitamin c + daily
radiance moisturizer

1.7 US FL OZ / 50 mL ℮

dermalogica